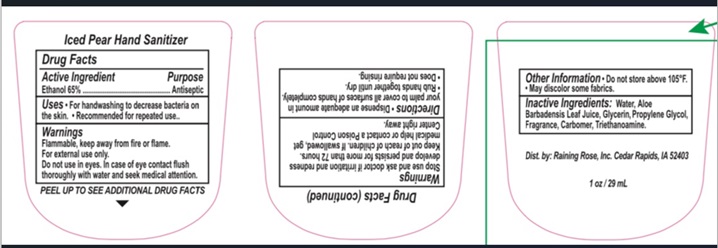 DRUG LABEL: Hand Sanitizer
NDC: 65692-1002 | Form: GEL
Manufacturer: Raining Rose, Inc.
Category: otc | Type: HUMAN OTC DRUG LABEL
Date: 20231103

ACTIVE INGREDIENTS: ALCOHOL 65 mL/100 mL
INACTIVE INGREDIENTS: WATER; ALOE VERA LEAF; GLYCERIN; PROPYLENE GLYCOL; CARBOMER INTERPOLYMER TYPE A (55000 CPS); TROLAMINE

Iced Pear Hand Sanitizer

Active Ingredient
Ethanol 65%

Purpose
Antiseptic

Warnings

Flammable, keep away from fire or flame.

For external use only.

Do not use in eyes. In case of eye contact flush thoroughly with water and seek medical attention.

Stop use and ask doctor if irritation and redness develops and persists for more than 72 hours.

Keep out of reach of children. If swallowed, get medical help or contact a Poison Control Center right away.

Directions

- Dispense an adequate amount in your palm to cover all surfaces of hands completely.
- Rub hands together until dry.
- Does not require rinsing.

INACTIVE INGREDIENT

Inactive Ingredients: Water, Aloe Barbadenis Leaf Juice, Glycerin, Propylene Glycol, Fragrance, Carbomer, Triethanolamine.

Uses

- For handwashing to decrease bacteria on the skin.
- Recommended for repeated use.

Other Information

- Do not store above 105 F
- May discolor some fabrics.

Product Label - Iced Pear Hand Sanitizer

Iced Pear Hand Sanitizer

1 oz / 29 mL

Dist by: Raining Rose, Inc. Cedar Rapids, IA52403

res